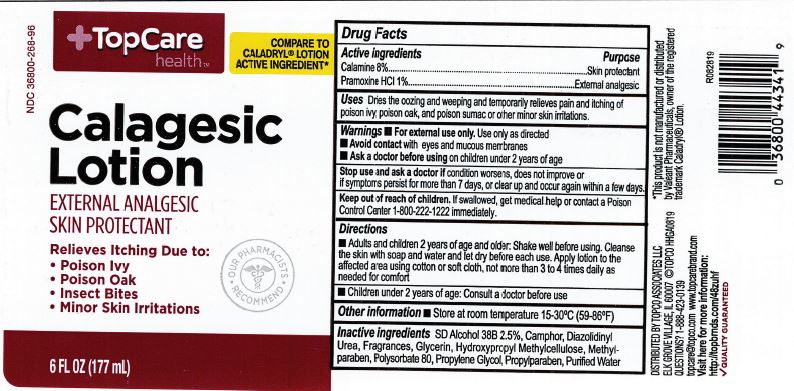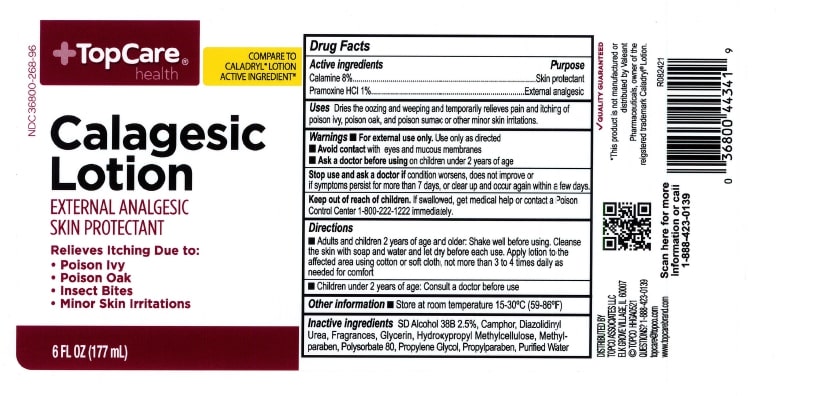 DRUG LABEL: TopCare Calagesic
NDC: 36800-268 | Form: LOTION
Manufacturer: TOPCO ASSOCIATES LLC
Category: otc | Type: HUMAN OTC DRUG LABEL
Date: 20231218

ACTIVE INGREDIENTS: ZINC OXIDE 80 mg/1 mL; PRAMOXINE HYDROCHLORIDE 10 mg/1 mL
INACTIVE INGREDIENTS: GLYCERIN; CAMPHOR (NATURAL); POLYSORBATE 80; PROPYLENE GLYCOL; DIAZOLIDINYL UREA; WATER; METHYLPARABEN; PROPYLPARABEN

Top Care Calagesic Lotion

ACTIVE INGREDIENT

Calamine 8%

Pramoxine Hydochloride 1%

PURPOSE

Skin Protectant

External analgesic

INDICATIONS AND USAGE

Dries the oozing and weeping, and temporarily relieves pain and itching of poison ivy, oak, and sumac or other skin irritations.

WARNINGS

For external use only. Use only as directed.

When using this product. Avoid contact with eyes and moucous membranes.

KEEP OUT OF REACH OF CHILDREN

In case of accidental ingestion, seek profesional assistance or contact a Poison Control Center immediately.

DOSAGE AND ADMINISTRATION

Adults and children 2 yr. of age and older. Shake well before using. Cleanse the skin with soap and water and let dry. Apply to the affected area using cotton or soft cloth, not more than 3 to 4 times daily as needed for comfort.

Children under 2 yrs. of age. Consult a doctor before use.

INACTIVE INGREDIENT

SD Alcohol 38B 2.5%, Camphor, Diazolidinyl Urea, Fragrances, Glycerin, Hydroxypropyl Methycelulose, Methylparaben, Polysorbate 80, Propylene Glycol, Propylparaben and Purified Water.